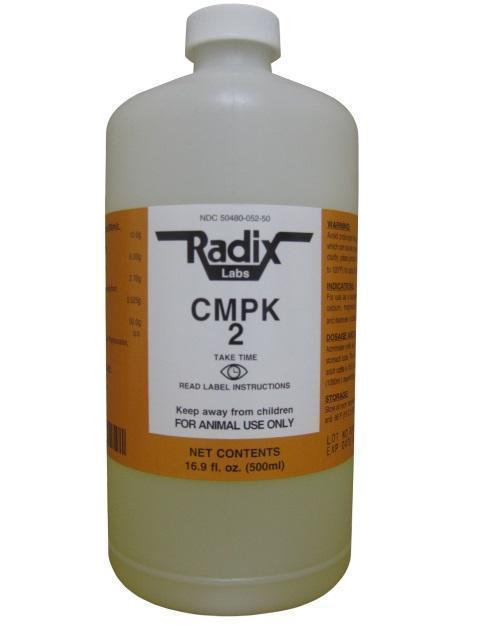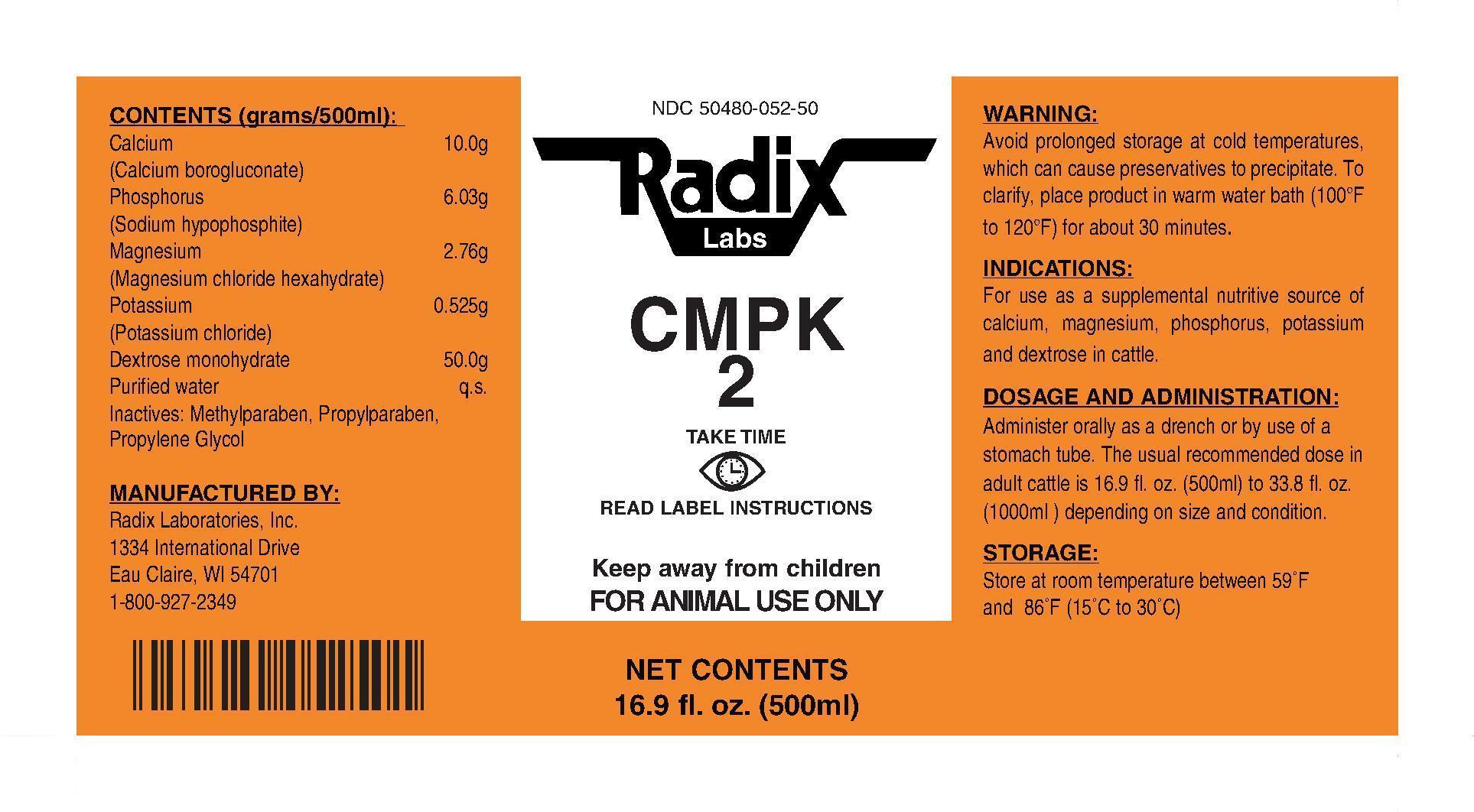 DRUG LABEL: CMPK2
NDC: 50480-052 | Form: LIQUID
Manufacturer: Radix Laboratories, Inc.
Category: animal | Type: OTC ANIMAL DRUG LABEL
Date: 20140324

ACTIVE INGREDIENTS: CALCIUM BOROGLUCONATE 2 g/100 mL; SODIUM HYPOPHOSPHITE 1.2 g/100 mL; MAGNESIUM CHLORIDE 0.552 g/100 mL; POTASSIUM CHLORIDE 0.105 g/100 mL; DEXTROSE MONOHYDRATE 10 g/100 mL

CMPK2

• CONTENTS (grams/500ml):

- Calcium ............................10.0g
- (Calcium Borogluconate)
- Phosphorus.......................6.03g
- (Sodium Hypophosphite)
- Magnesium........................2.76g
- (Magnesium Chloride Hexahydrate)
- Potassium........................0.525g
- (Potassium Chloride)
- Dextrose Monohydrate......50.0g

Indications:

- For use as a supplemental nutritive source of calcium, phosphorus, magnesium, potassium and dextrose in cattle.

Storage:

- Store at controlled room temperature between 59oF to 86oF (15oC -30oC).

Warnings:

- Avoid storage at cold temperatures which can cause product to become cloudy.
- To clarify place product in warm water bath (100oF-120oF) for about 30 minutes.

Dosage and administration:

- Administer orally as a drench or by use of a stomach tube.
- The usual recommended dose in adult cattle is 16.9 fl. oz (500mL) to 33.8 fl.oz (1000mL) depending on size and condition.

- Keep away from children.